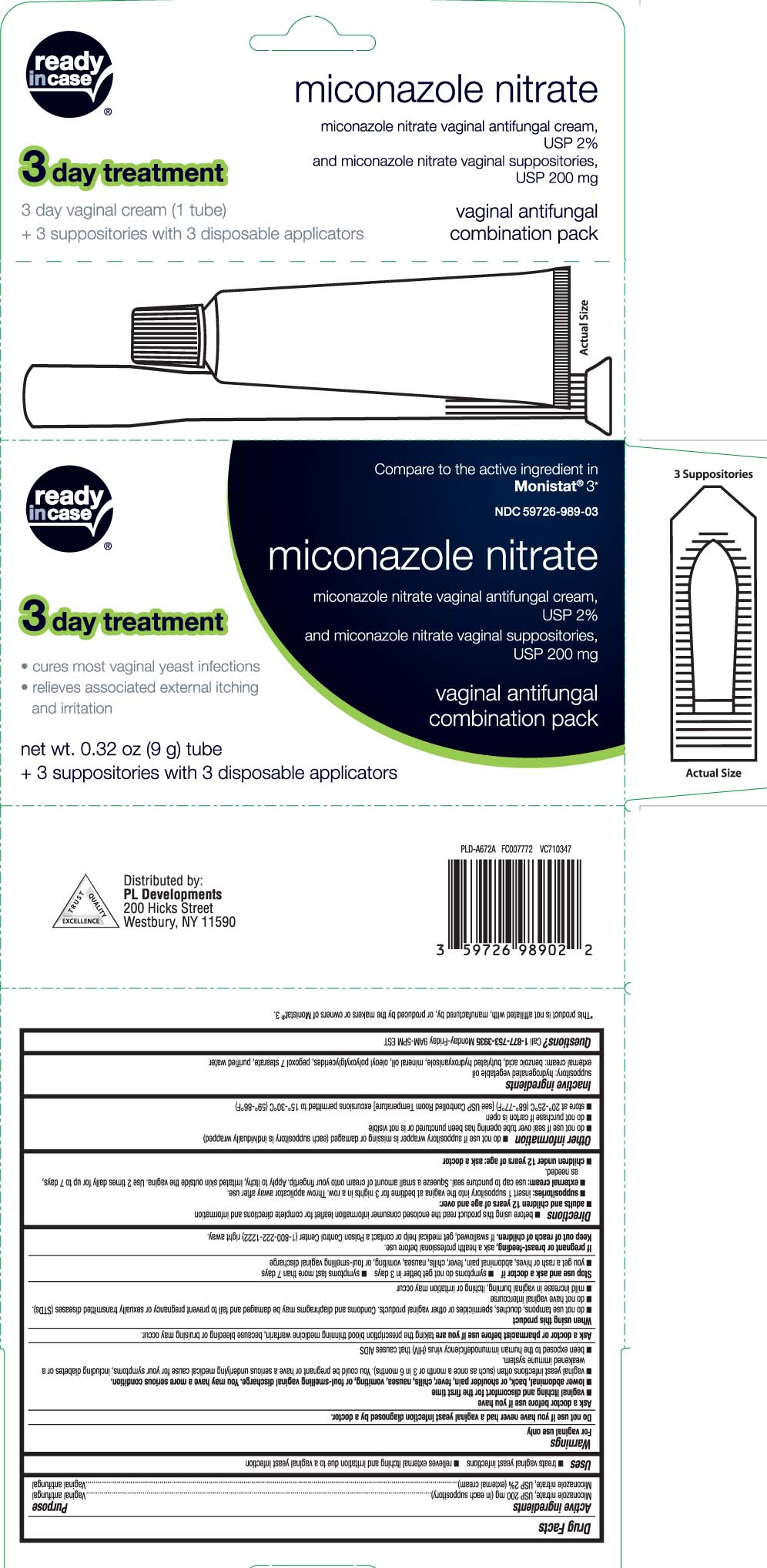 DRUG LABEL: Miconazole 3 Combination Pack
NDC: 59726-989 | Form: KIT | Route: VAGINAL
Manufacturer: P & L Development, LLC
Category: otc | Type: HUMAN OTC DRUG LABEL
Date: 20241105

ACTIVE INGREDIENTS: MICONAZOLE NITRATE 10 mg/0.5 g; MICONAZOLE NITRATE 200 mg/1 1
INACTIVE INGREDIENTS: BENZOIC ACID; BUTYLATED HYDROXYANISOLE; MINERAL OIL; APRICOT KERNEL OIL PEG-6 ESTERS; PEGOXOL 7 STEARATE; WATER; HYDROGENATED PALM KERNEL OIL

Miconazole 3 Combination Pack

Active ingredients

Miconazole nitrate, USP 200 mg (in each suppository)
Miconazole nitrate, USP 2% (external cream)

Purpose

Vaginal antifungal

Vaginal antifungal

Uses

- treats vaginal yeast infections
- relieves external itching and irritation due to a vaginal yeast infection

Warnings

For vaginal use only

Do not use

if you have never had a vaginal yeast infection diagnosed by a doctor.

Ask a doctor before use if you have

- vaginal itching and discomfort for the first time
- lower abdominal, back or shoulder pain, fever, chills, nausea, vomiting, or foul-smelling vaginal discharge. You may have a more serious condition.
- vaginal yeast infections often (such as once a month or 3 in 6 months). You could be pregnant or have a serious underlying medical cause for your symptoms, including diabetes or a weakened immune system.
- been exposed to the human immunodeficiency virus (HIV) that causes AIDS

Ask a doctor or pharmacist before use if you are

taking the prescription blood thinning medicine warfarin, because bleeding or bruising may occur

When using this product

- do not use tampons, douches, spermicides or other vaginal products. Condoms and diaphragms may be damaged and fail to prevent pregnancy or sexually transmitted diseases (STDs)
- do not have vaginal intercourse
- mild increase in vaginal burning, itching or irritation may occur

Stop use and ask a doctor if

- symptoms do not get better in 3 days
- symptoms last more than 7 days
- you get a rash or hives, abdominal pain, fever, chills, nausea, vomiting, or foul-smelling vaginal discharge

If pregnant or breast-feeding,

ask a health professional before use.

Keep out of reach of children.

If swallowed, get medical help or contact a Poison Control Center (1-800-222-1222) right away.

Directions

- before using this product read the enclosed consumer information leaflet for complete directions and information
- adults and children 12 years of age and over:
  - suppositories: insert 1 suppository into the vagina at bedtime for 3 nights in a row. Wash applicator away after use.
  - external cream: Use cap to puncture seal. Squeeze a small amount of cream onto your fingertip. Gently apply the cream onto the itchy, irritated skin outside the vagina. Use 2 times daily for up to 7 days, as needed.
- children under 12 years of age: ask a doctor

Other information

- do not use if suppository wrapper is missing or damaged (each suppository is individually wrapped)
- do not use if seal over tube opening has been punctured or is not visible
- do not purchase if carton is open
- store at 20º - 25ºC (68º - 77ºF) [see USP controlled Room Temperature] excursions permitted to 15°-30°C (59°-86°F)

Inactive ingredients

- suppository: hydrogenated vegetable oil
- external cream: benzoic acid, butylated hydroxyanisole, mineral oil, oleoyl polyoxylglycerides, pegoxol 7 stearate, purified water

Questions?

Call 1-877-753-3935 Monday-Friday 9AM-5PM EST

Principal Display Panel

Compare to the active ingredient in Monistat® 3*

miconazole nitrate

Miconazole nitrate vaginal antifungal cream, USP 2%

and Miconazole nitrate vaginal suppositories, USP 200 mg

vaginal antifungal

combination pack

3 day treatment

- Cures most vaginal yeast infections
- Relieves associated external itching and irritation

net wt. oz (g) tube

+ 3 suppositories with 3 disposable applicators

*This product is not affiliated with, manufactured by, or produced by the makers or owners of Monistat® 3.

Distributed by:

PL Developments

200 Hicks Street

Westbury, NY 11590

Package Label

READYinCASE Miconazole Nitrate Combination